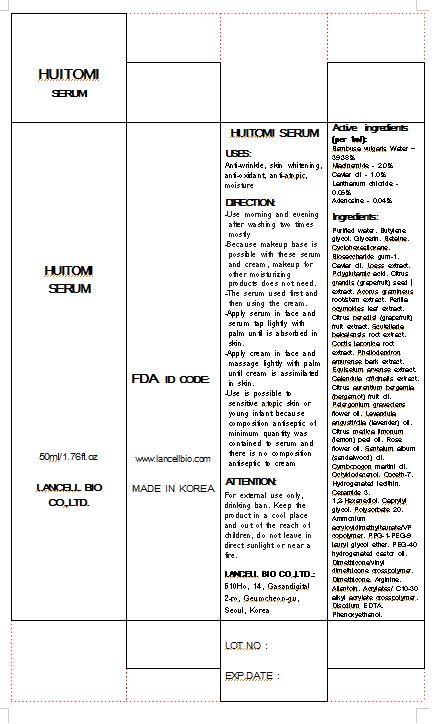 DRUG LABEL: HUITOMI SERUM
NDC: 69388-5001 | Form: LIQUID
Manufacturer: Lancell Bio Co., Ltd.
Category: otc | Type: HUMAN OTC DRUG LABEL
Date: 20141201

ACTIVE INGREDIENTS: GLYCERIN 5 g/100 mL
INACTIVE INGREDIENTS: WATER; LANTHANUM CHLORIDE; ADENOSINE

Drug Facts

ACTIVE INGREDIENT

glycerine

INACTIVE INGREDIENT

■Purified water ■Butylene glycol ■Glycerin ■Betaine ■Cyclohexasiloxane ■Biosaccharide gum-1 ■Caviar oil ■Loess extract ■Polyglutamic acid ■Citrus grandis (grapefruit) seed extract ■Acorus gramineus root/stem extract ■Perilla ocymoides leaf extract ■Citrus paradisi (grapefruit) fruit extract ■Scutellaria baicalensis root extract ■Coptis japonica root extract ■Phellodendron amurense bark extract ■Equisetum arvense extract ■Calendula officinalis extract ■Citrus aurantium bergamia (bergamot) fruit oil ■Pelargonium graveolens flower oil ■Lavandula angustifolia (lavender) oil ■Citrus medica limonum (lemon) peel oil ■Rose flower oil ■Santalum album (sandalwood) oil ■Cymbopogon martini oil ■Octyldodecanol ■Coceth-7 ■Hydrogenated lecithin ■Ceramide 3 ■1,2-Hexanediol ■Caprylyl glycol ■Polysorbate 20 ■Ammonium acryloyldimethyltaurate/VP copolymer ■PPG-1-PEG-9 lauryl glycol ether ■PEG-40 hydrogenated castor oil ■Dimethicone/vinyl dimethicone crosspolymer ■Dimethicone ■Arginine ■Allantoin ■Acrylates/C10-30 alkyl acrylate crosspolymer ■Disodium EDTA ■Phenoxyethanol

PURPOSE

Anti-wrinkle, skin whitening, anti-oxidant, anti-atopic, moisture

keep out of reach of children

INDICATIONS AND USAGE

Use morning and evening after washing two times mostly
Because makeup base is possible with these serum and cream, makeup for other moisturizing products does not need.
The serum used first and then using the cream.
Apply serum in face and serum tap lightly with palm until is absorbed in skin.
Apply cream in face and massage lightly with palm until cream is assimilated in skin.
Use is possible to atopic sensitive skin or young infant because composition antiseptic of minimum quantity was contained to serum and there is no composition antiseptic to cream

WARNINGS

For external use only, drinking ban
keep in a cool place

DOSAGE AND ADMINISTRATION

for external use only